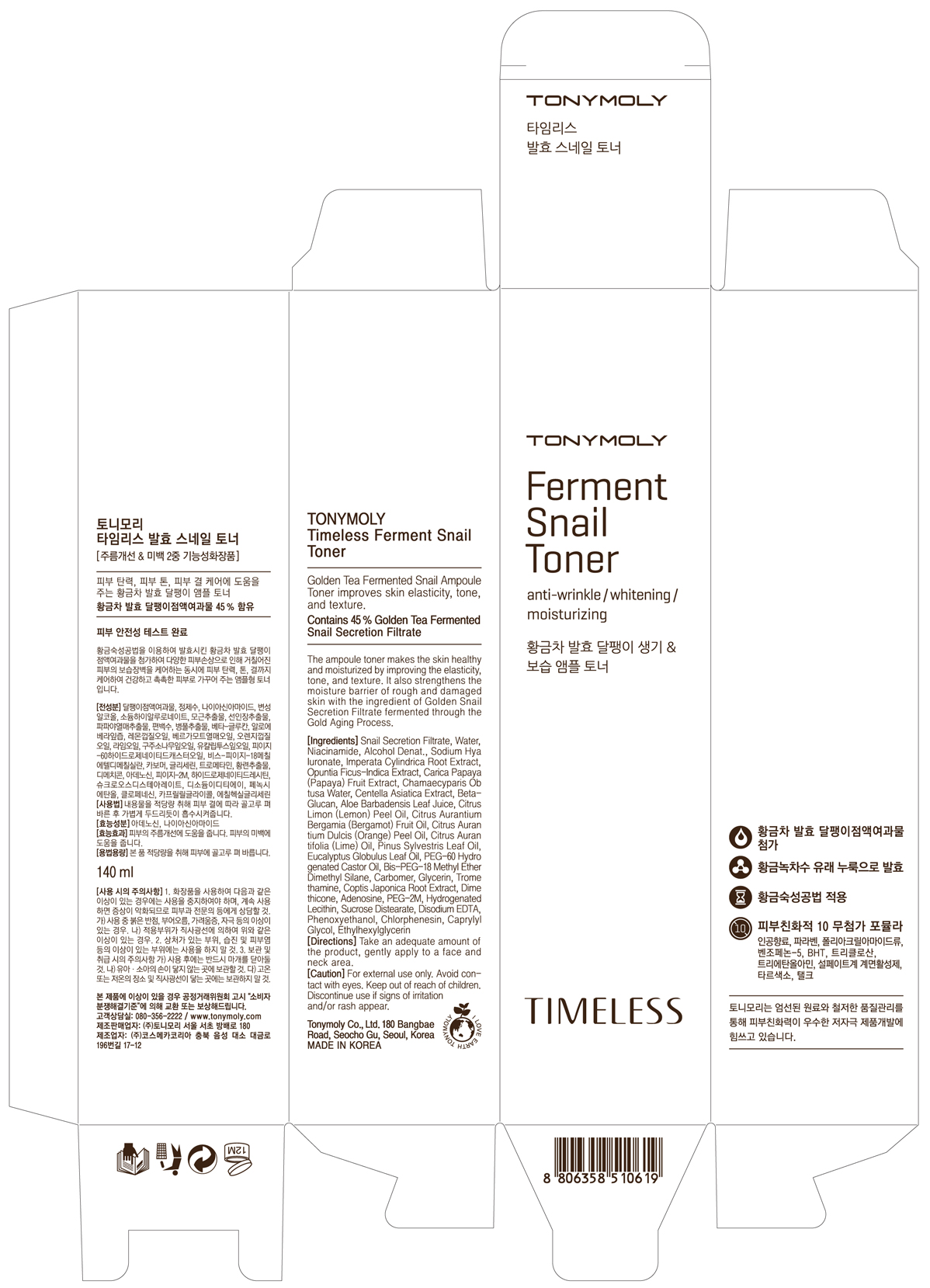 DRUG LABEL: TONYMOLY Timeless Ferment Snail Toner
NDC: 59078-100 | Form: LIQUID
Manufacturer: Tonymoly Co., Ltd.
Category: otc | Type: HUMAN OTC DRUG LABEL
Date: 20160202

ACTIVE INGREDIENTS: GLYCERIN 1762.6 mg/140 mL
INACTIVE INGREDIENTS: IMPERATA CYLINDRICA ROOT; LEMON PEEL; BERGAMOT OIL; ALOE VERA LEAF; PAPAYA; WATER; BIS-PEG-18 METHYL ETHER DIMETHYL SILANE; CAPRYLYL GLYCOL; SUCROSE DISTEARATE; ADENOSINE; ALCOHOL; PROPANEDIOL; COPTIS JAPONICA ROOT; POTASSIUM SORBATE; SODIUM BENZOATE; BUTYLENE GLYCOL; NIACINAMIDE; PEG-60 HYDROGENATED CASTOR OIL; TROMETHAMINE; PHENOXYETHANOL; CHLORPHENESIN; DIMETHICONE; ETHYLHEXYLGLYCERIN; POLYETHYLENE OXIDE 100000; CHAMAECYPARIS OBTUSA WHOLE; OPUNTIA FICUS-INDICA; ORANGE OIL; LIME OIL; EUCALYPTUS OIL; HYDROGENATED SOYBEAN LECITHIN; HYALURONATE SODIUM; POLYETHYLENE GLYCOL 400; PINE NEEDLE OIL (PINUS SYLVESTRIS); CENTELLA ASIATICA

Active Ingredients

Glycerin 1.00%

Purpose

Skin Protectant

Use

Golden Tea Fermented Snail Ampoule Toner improves skin elasticity, tone, and texture.

Contains 45% Golden Tea Fermented Snail Secretion Filtrate

The ampoule toner makes the skin healthy and moisturized by improving the elasticity, tone, and texture. It also strengthens the moisture barrier of rough and damaged skin with the ingredient of Golden Snail Secretion Filtrate fermented through the Gold Aging Process.

Caution

For external use only. Avoid contact with eyes. Keep out of reach of children. Discontinue use if signs of irritation and/or rash appear.

Keep out of reach of children. Discontinue use if signs of irritation and/or rash appear.

Directions

Take an adequate amount of the product, gently apply to a face and neck area.

Inactive Ingredients

Water, Snail Secretion Filtrate, Butylene Glycol, Alcohol Denat., Niacinamide, PEG-60 Hydrogenated Castor Oil, Carbomer, Tromethamine, Phenoxyethanol, Chlorphenesin, Bis-PEG-18 Methyl Ether Dimethyl Silane, Dimethicone, Ethylhexylglycerin, PEG-2M, Caprylyl Glycol, Chamaecyparis Obtusa Water, Hydrogenated Lecithin, Sucrose Distearate, Imperata Cylindrica Root Extract, Adenosine, Alcohol, Disodium EDTA, Opuntia Ficus-Indica Extract, Citrus Medica Limonum (Lemon) Peel Oil, Propanediol, Coptis Japonica Root Extract, Citrus Aurantium Bergamia (Bergamot) Fruit Oil, Sodium Hyaluronate, PEG-8, Citrus aurantium dulcis (orange) peel oil, Citrus Aurantifolia (Lime) Oil, Pinus Sylvestris Leaf Oil, Centella Asiatica Extract, Eucalyptus Globulus Leaf Oil, Aloe Barbadensis Leaf Juice, Carica papaya (papaya) fruit Extract, Beta-Glucan, Potassium sorbate, Sodium Benzoate